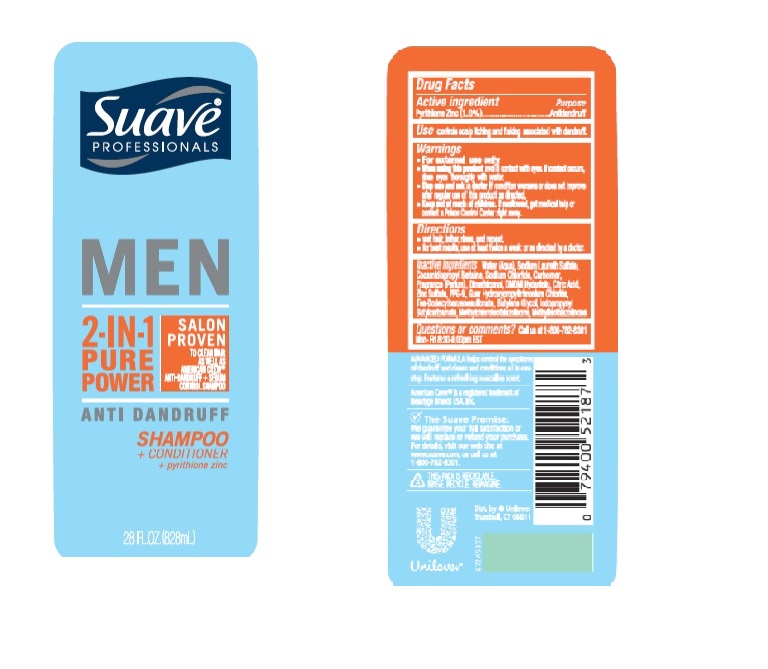 DRUG LABEL: Suave
NDC: 64942-1437 | Form: SHAMPOO
Manufacturer: Conopco Inc. d/b/a Unilever
Category: otc | Type: HUMAN OTC DRUG LABEL
Date: 20210312

ACTIVE INGREDIENTS: PYRITHIONE ZINC 1 g/100 mL
INACTIVE INGREDIENTS: ZINC SULFATE; CARBOMER HOMOPOLYMER, UNSPECIFIED TYPE; WATER; SODIUM LAURETH SULFATE; COCAMIDOPROPYL BETAINE; SODIUM CHLORIDE; DMDM HYDANTOIN; TRIETHANOLAMINE DODECYLBENZENESULFONATE; CITRIC ACID MONOHYDRATE; PPG-9; METHYLCHLOROISOTHIAZOLINONE; METHYLISOTHIAZOLINONE; GUAR HYDROXYPROPYLTRIMONIUM CHLORIDE (1.7 SUBSTITUENTS PER SACCHARIDE); DIMETHICONOL (41 MPA.S); BUTYLENE GLYCOL; IODOPROPYNYL BUTYLCARBAMATE

Suave Men 2 in 1 Pure Power Anti Dandruff Shampoo and Conditioner

Active Ingredient

Pyrithione Zinc (1.0%)

Purpose

Antidandruff

Use

controls scalp itching and flaking associated with dandruff.

Warnings

• For external use only

• When using this product avoid contact with eyes. If contact occurs, rinse eyes thoroughly with water.

• Stop use and ask a doctor if condition worsens or does not improve after regular use of this product as directed.

• Keep out of reach of children. If swallowed, get medical help or contact a Poison Control Center right away.

Directions

• wet hair, lather, rinse, and repeat.

• for best results, use at least twice a week or as directed by a doctor.

Inactive Ingredients

Water (Aqua), Sodium Laureth Sulfate, Cocamidopropyl Betaine, Sodium Chloride, Carbomer, Fragrance (Parfum), Dimethiconol, DMDM Hydantoin, Citric Acid, Zinc Sulfate, PPG-9, Guar Hydroxypropyltrimonium Chloride, TEA-Dodecylbenzenesulfonate, Butylene Glycol, Iodopropynyl Butylcarbamate, Methylchloroisothiazolinone, Methylisothiazolinone.

Questions or comments?

Call us at 1-800-782-8301

Mon - Fri 8:30-6:00 pm EST